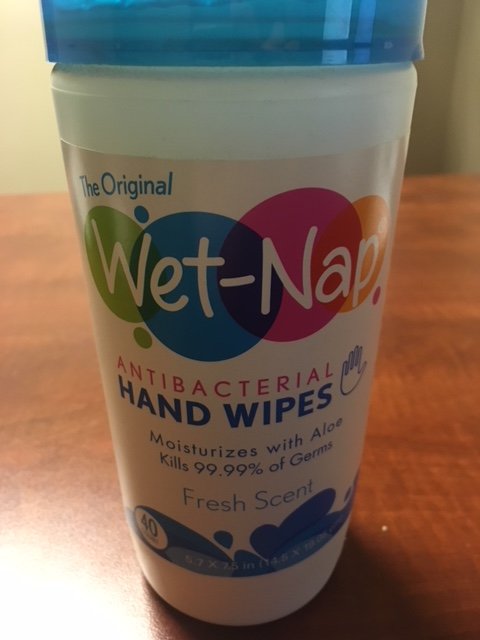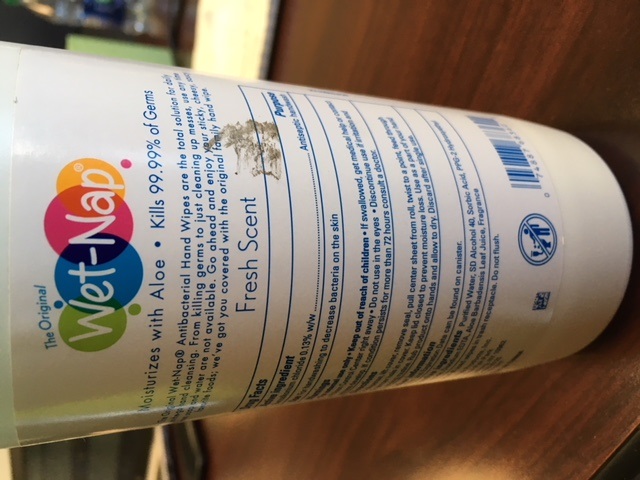 DRUG LABEL: Wet Naps Antibacterial Hand Wipes
NDC: 71928-7012 | Form: CLOTH
Manufacturer: Westrock Rkt Company
Category: otc | Type: HUMAN OTC DRUG LABEL
Date: 20171215

ACTIVE INGREDIENTS: BENZALKONIUM CHLORIDE 0.13 mg/1 mL
INACTIVE INGREDIENTS: ALCOHOL; SORBIC ACID; PPG-2 HYDROXYETHYL COCAMIDE; EDETATE DISODIUM; ALOE VERA LEAF; WATER

Warning section

For external use only. Keep out of reach of children. If swallowed get medical help or contact a posion control center right away. Do not use in eyes. Discontinue use if irritation develop. If condition persists for more than 72 hours consult a doctor.

INACTIVE INGREDIENT

Purified water, SD alcohol 40, Sorbic Acid, PPG-2 Hydroxyethyl Cocamide, Disodium EDTA, Aloe Barbadensis leaf join, Fragrance

Directions

To dispense, life cover, remove seal, pull center sheet from toll, twist to point, feed through dispenser hole in cover. Keep lid closed to prevent moisture loss. Use as a part of your cleaning routine. Rub product onto hands and allow to dry. Discard after single use.

Keep out of reach of children.

PURPOSE

Antiseptic handwash

ACTIVE INGREDIENT

Benzalkonium chloride 0.13% mg/ml

DOSAGE AND ADMINISTRATION

Strength Benzalkonium chloride 0.13% mg/ml

Cloth wipe administraion

handwipe.jpg

Consumer facing image of hand wipes.